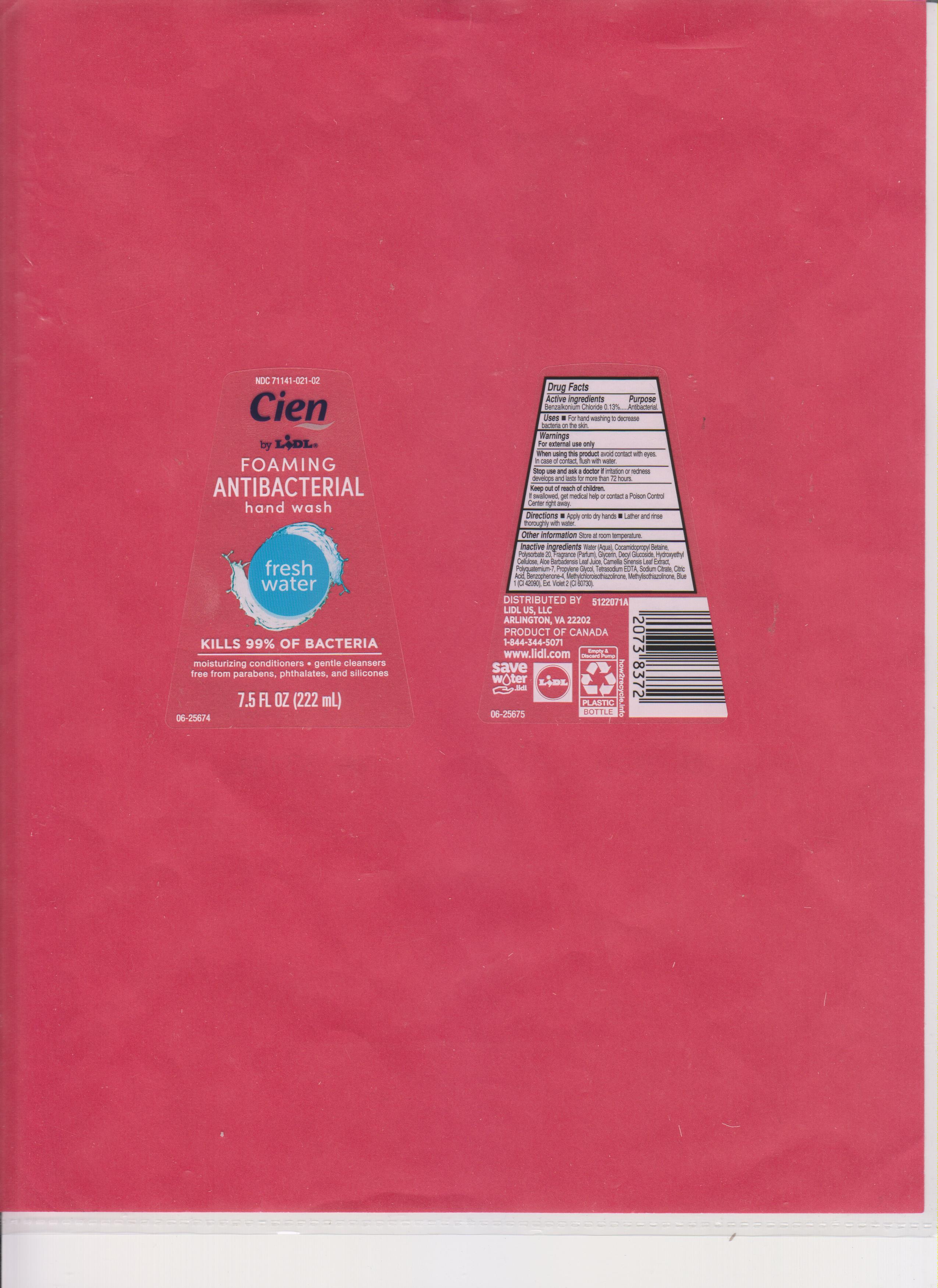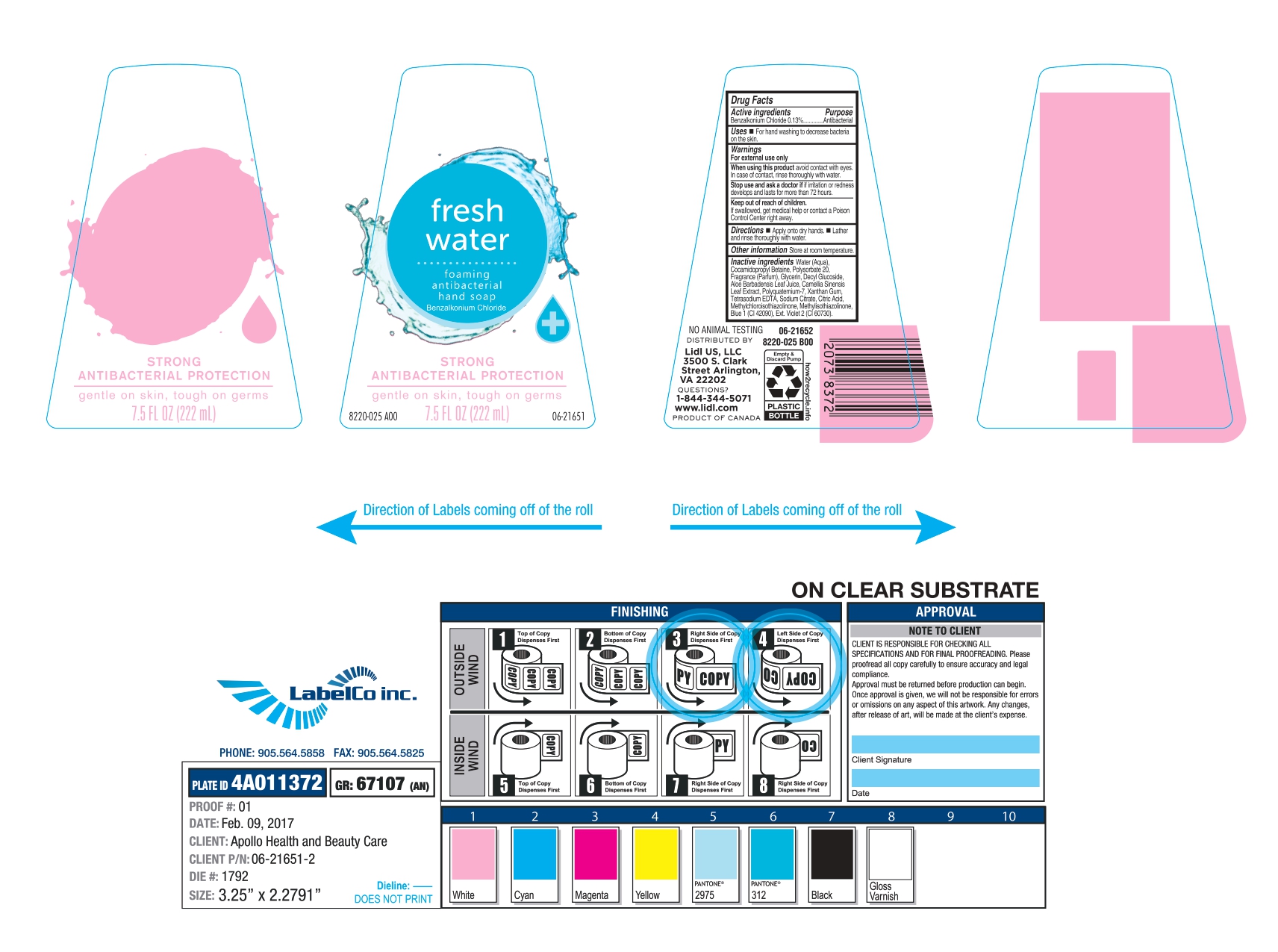 DRUG LABEL: LIDL
NDC: 71141-021 | Form: SOAP
Manufacturer: LIDL US LLC
Category: otc | Type: HUMAN OTC DRUG LABEL
Date: 20250206

ACTIVE INGREDIENTS: BENZALKONIUM CHLORIDE 130 mg/100 mL
INACTIVE INGREDIENTS: HYDROXYETHYL CELLULOSE, UNSPECIFIED; PROPYLENE GLYCOL; FD&C BLUE NO. 1; EXT. D&C VIOLET NO. 2; METHYLCHLOROISOTHIAZOLINONE; WATER; METHYLISOTHIAZOLINONE; FRAGRANCE CLEAN ORC0600327; CITRIC ACID; EDETATE SODIUM; SODIUM CITRATE; COCAMIDOPROPYL BETAINE; POLYSORBATE 20; GLYCERIN; DECYL GLUCOSIDE; ALOE VERA LEAF; CAMELLIA SINENSIS LEAF; BENZOPHENONE-4; POLYQUATERNIUM-7

71141-021-02, LIDL US LLC

Active Ingredient.

Benzalkonium Chloride (0.13%)

Purpose

Antibacterial

Uses

- For Hand washing to decrease bacteria on the skin

Warnings

For external use only

When using this product

Avoid contact with eyes. In case of contact, rinse thoroughly with water.

Stop use and ask a doctor

If irritation or redness develops and lasts for more than 72 hours

Keep out of reach of children.

If swallowed, get medical help or contact a Poison Control Center right away.

Directions

- Apply onto dry hands
- Lather and rinse thoroughly with water.

Other Information

Store at room temperature

Inactive Ingredients

Water (Aqua), Cocamidopropyl Betaine, Polysorbate 20, Fragrance (Parfum), Glycerin, Decyl Glucoside, Hydroxyethyl cellulose, Aloe Barbadensis Leaf Juice, Camellia Sinensis Leaf Extract, Polyquatermium-7, Propylene Glycol, Tetrasodium EDTA, Sodium Citrate, Citric Acid, Benzophenone-4, Methylchloroisothiazolinone, Methylisothiazolinone, Blue 1 (Cl42090), Ext Violet 2 (Cl 60730).